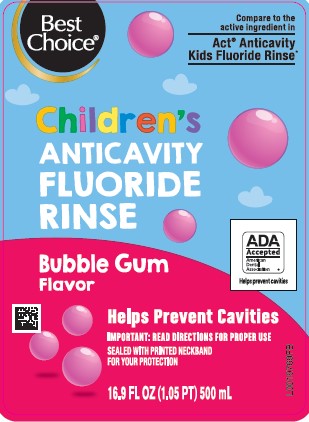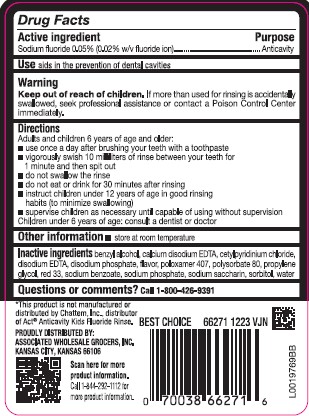 DRUG LABEL: Anticavity Rinse
NDC: 63941-904 | Form: MOUTHWASH
Manufacturer: Valu Merchandisers Company
Category: otc | Type: HUMAN OTC DRUG LABEL
Date: 20260216

ACTIVE INGREDIENTS: SODIUM FLUORIDE 0.2 mg/1 mL
INACTIVE INGREDIENTS: BENZYL ALCOHOL; EDETATE CALCIUM DISODIUM ANHYDROUS; CETYLPYRIDINIUM CHLORIDE; EDETATE DISODIUM; SODIUM PHOSPHATE, DIBASIC, ANHYDROUS; POLOXAMER 407; POLYSORBATE 80; PROPYLENE GLYCOL; D&C RED NO. 33; SODIUM BENZOATE; SODIUM PHOSPHATE; SACCHARIN SODIUM; SORBITOL; WATER

Best Choice 004.002/004AE
Anticavity Fluoride Rinse, Bubble Gum

Active ingredient

Sodium Fluoride 0.05% (0.2% w/v fluoride ion)

Purpose

Anticavity

Use

aids in the prevention of dental cavities

Warnings

for this product

Keep out of reach of children.

If more than used for rinsing is accidentally swallowed, seek professional assistance or contact a Poison Control Center immediately.

Directions

Adults and children 6 years of age and older:

- use once a day after brushing your teeth with a toothpaste
- vigorously swish 10 milliliters of rinse between your teeth for 1 minute and then spit out
- do not swallow the rinse
- do not eat or drink for 30 minutes after rinsing
- instruct children under 12 years of age in good rinsing habits (to minimize swallowing)
- supervise children as necessary until capable of using without supervision

Children under 6 years of age: consult a dentist or doctor

Other information

store at room temperature

Inactive ingredients

benzyl alcohol, calcium disodium EDTA, cetylpyridinium chloride, disodium EDTA, disodium phosphate, flavor, poloxamer 407, polysorbate 80, propylene glycol, red 33, sodium benzoate, sodium phosphate, sodium saccharin, sorbitol, water

Disclaimer

*This product is not manufactured or distributed by Chattem, Inc., distributer of Act®Anticavity Kids Fluoride Rinse.

Adverse reaction

PROUDLY DISTRIBUTED BY:

ASSOCIATED WHOLESALE GROCERS, INC.

KANSAS CITY, KANSAS 66106

Scan here for more product information.

Call 1-844-292-1112 for more product information.

Principal display panel

Best Choice®

Compare to the active ingredient in Act®Anticavity Kids Fluoride Rinse*

Children's ANTICAVITY FLUORIDE RINSE

Bubble Gum Flavor

ADA Accepted

American Dental Association

Helps prevent cavities

Helps Prevent Cavities

IMPORTANT: READ DIRECTIONS FOR PROPER USE

SEALED WITH PRINTED NECKBAND FOR YOUR PROTECTION

16.9 FL OZ (1.05 PT) 500 mL